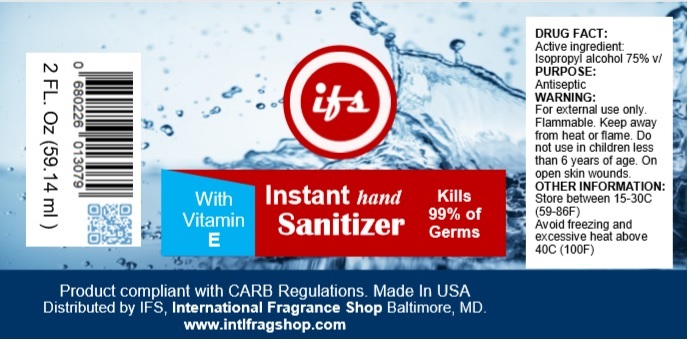 DRUG LABEL: Instant hand Sanitizer
NDC: 74462-143 | Form: SPRAY
Manufacturer: International Fragrances Inc
Category: otc | Type: HUMAN OTC DRUG LABEL
Date: 20200415

ACTIVE INGREDIENTS: ISOPROPYL ALCOHOL 75 mL/100 mL
INACTIVE INGREDIENTS: WATER; .ALPHA.-TOCOPHEROL; ALOE VERA LEAF

Instant hand Sanitizer

Active ingredient:

Isopropyl alcohol 75% v/v

PURPOSE:

Antiseptic

Uses

- hand sanitizer to decrease bacteria on the skin
- recommended for repeated use
- for use when soap and water are not available

WARNING:

For external use only. Flammable. Keep away from heat or flame. Do not use in children less than 6 years of age. On open skin wounds.

Keep out of reach of children.

Directions

- wet hands thoroughly with product and allow to dry without wiping.
- supervise children under 6 years of age when using this product to avoid swallowing

OTHER INFORMATION:

Store between 15-30C (59-86F)

Avoid freezing and excessive heat above 40C (100F)

Inactive ingredients

Water, Vitamin E, Aloe Vera

With Vitamin E

Kills 99% of Germs

Product compliant with CARB Regulations. Made in USA

Distributed by IFS, International Fragrance Shop Baltimore, MD.

www.intlfragshop.com